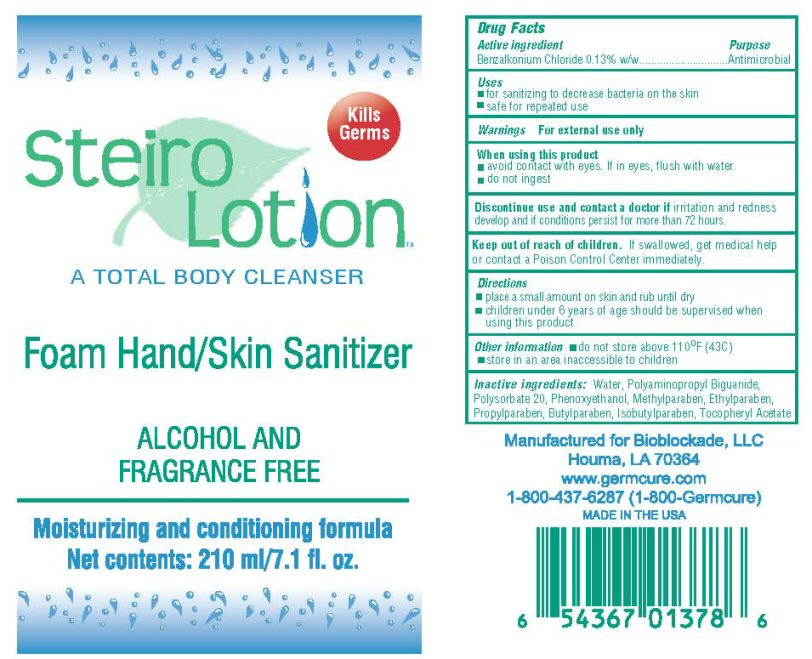 DRUG LABEL: Steiro
NDC: 76079-001 | Form: LIQUID
Manufacturer: Bioblockade LLC
Category: otc | Type: HUMAN OTC DRUG LABEL
Date: 20110323

ACTIVE INGREDIENTS: BENZALKONIUM CHLORIDE 0.13 mL/100 mL
INACTIVE INGREDIENTS: WATER; ALPHA-TOCOPHEROL ACETATE; POLYSORBATE 20; PHENOXYETHANOL; METHYLPARABEN; ETHYLPARABEN; PROPYLPARABEN; BUTYLPARABEN; ISOBUTYLPARABEN; POLYAMINOPROPYL BIGUANIDE

Active Ingredient

Benzalkonium Chloride 0.13%

Inactive Ingredients

Water, Tocopheryl Acetate, Polysorbate 20, Polyaminopropyl Biguanide, Phenooxythanol, Methylparaben, Ethylparaben, Propylparaben, Butylparaben, and Isobutylparaben

Purpose

Antimicrobial

Uses

For Sanitizing to decrease bacteria on the skin, safe for repeated use

Directions

Place a small amount on skin and rub until dry.

Keep Out of Reach of Children

Children under 6 years of age should be supervised when using this product.

Warning

For external use only. When using this product avoid contact with the eyes. If in eyes flush with water. Do not ingest. Discontinue use and contact a doctor if irritation and redness develop and if conditions persist for more than 72 hours.

Other Information

Do not store above 110 degrees F (43 C) store in an area inaccessible to children.

Package Label

Steiro Lotion Kills Germs A Total Hand / Skin Sanitizer Foam Hand / Skin Sanitizer Alcohol and Fragrance Free Moisturizing and conditioning formula Net Contents: 210 ml/7.1 fl.oz.

Manufactured for Bioblockade LLC Houma, LA 70364